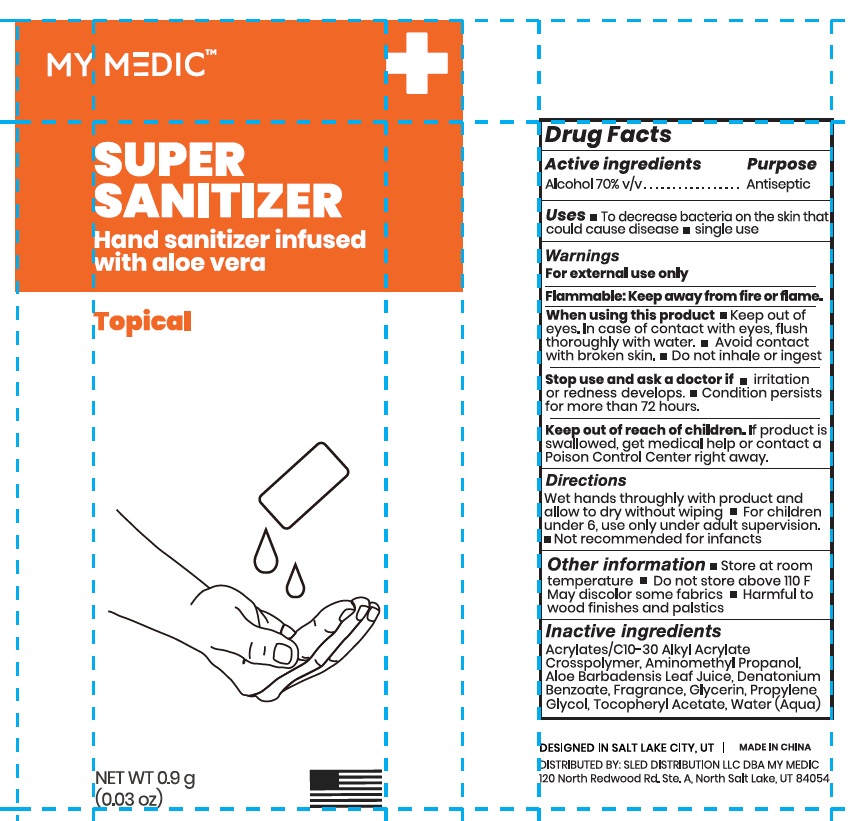 DRUG LABEL: MY MEDIC SUPER SANITIZER
NDC: 43473-057 | Form: GEL
Manufacturer: Nantong Health & Beyond Hygienic Products Inc.
Category: otc | Type: HUMAN OTC DRUG LABEL
Date: 20241002

ACTIVE INGREDIENTS: ALCOHOL 70 mL/100 mL
INACTIVE INGREDIENTS: WATER; GLYCERIN; PROPYLENE GLYCOL; ACRYLATES/C10-30 ALKYL ACRYLATE CROSSPOLYMER (60000 MPA.S); .ALPHA.-TOCOPHEROL ACETATE, D-; DENATONIUM BENZOATE; ALOE VERA LEAF; AMINOMETHYL PROPANEDIOL

43473-057 My Medic Super Sanitizer

Active ingredient

Alcohol 70% v/v

Purpose Antiseptic

Uses

- to decrease bacteria on the skin thatcould cause disease
- single use

Warnings

For external use only.

Flammable: keep away from fire or flames

When using this product:

- Keep out of eyes. in case of contact with eyes, flush thoroughly with water.
- Avoid contact with broken skin.
- Do not inhale or ingest.

Stop use and ask a doctor if:

- irritation orredness develops.
- Condition persists formore than 72 hours.

Keep out of reach of children. If product is swallowed, get medical help or contact a Poison Control Center right away.

Directions:
Wet hands thoroughly with product and allow to dry without wiping

- For children under 6, use only under adult supervision.
- Not recommended for infants

Other information

- Store at room temperature
- Do not store above 110F
- May discolor some fabrics
- Harmful to wood finishes and plastics

Inactive ingredients

Acrylates/C10-30Alkyl Acrylate Crosspolymer, Aminomethyl Propanol, Aloe Barbadensis Leaf Juice, Denatonium Benzoate, Fragrance, Glycerin, Propylene Glycol, Tocopheryl Acetate, Water (Aqua).